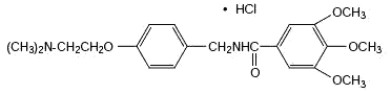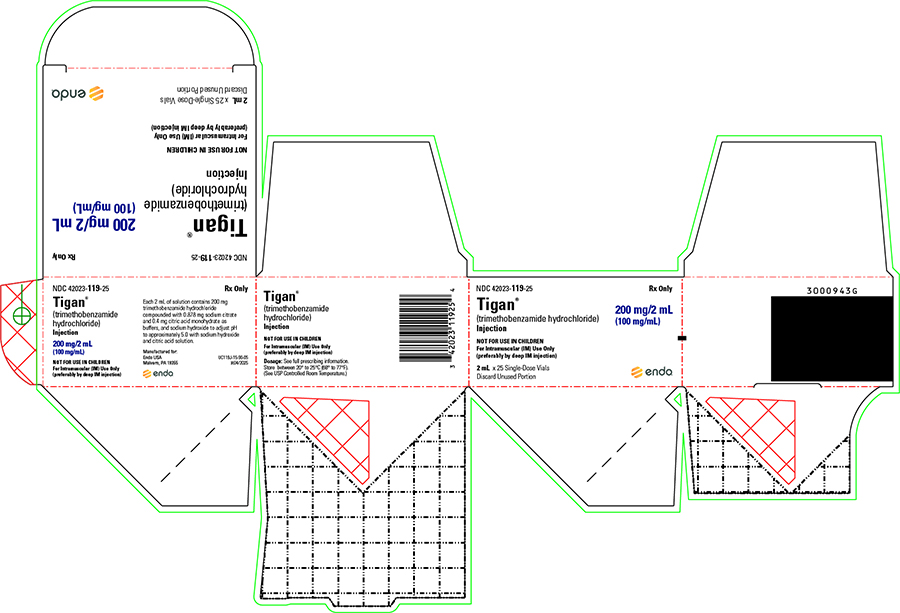 DRUG LABEL: Tigan
NDC: 42023-119 | Form: INJECTION
Manufacturer: Par Health USA, LLC
Category: prescription | Type: HUMAN PRESCRIPTION DRUG LABEL
Date: 20251114

ACTIVE INGREDIENTS: TRIMETHOBENZAMIDE HYDROCHLORIDE 100 mg/1 mL
INACTIVE INGREDIENTS: SODIUM CITRATE 0.5 mg/1 mL; CITRIC ACID MONOHYDRATE 0.2 mg/1 mL

Tigan®

(trimethobenzamide hydrochloride)

Injection

For Intramuscular Use Only

Not for Use in Pediatric Patients

DESCRIPTION

Chemically, trimethobenzamide hydrochloride (HCl) is N-[p-[2-(dimethylamino)ethoxy]benzyl]-3,4,5-trimethoxybenzamide monohydrochloride. It has a molecular weight of 424.93 and the following structural formula:

Single Dose Vials: Each 2-mL single-dose vial contains 200 mg trimethobenzamide hydrochloride compounded with 0.878 mg sodium citrate and 0.4 mg citric acid monohydrate as buffers and pH adjusted to approximately 5.0 with sodium hydroxide and citric acid solution.

CLINICAL PHARMACOLOGY

Mechanism of Action

The mechanism of action of Tigan® as determined in animals is obscure, but may involve the chemoreceptor trigger zone (CTZ), an area in the medulla oblongata through which emetic impulses are conveyed to the vomiting center; direct impulses to the vomiting center apparently are not similarly inhibited. In dogs pretreated with trimethobenzamide HCl, the emetic response to apomorphine is inhibited, while little or no protection is afforded against emesis induced by intragastric copper sulfate.

Pharmacokinetics

The pharmacokinetics of trimethobenzamide have been studied in healthy adult subjects. Following administration of 200 mg (100 mg/mL) Tigan IM injection, the time to reach maximum plasma concentration (Tmax) was about half an hour, about 15 minutes longer for Tigan 300 mg oral capsule than an IM injection. A single dose of Tigan 300 mg oral capsule provided a plasma concentration profile of trimethobenzamide similar to Tigan 200 mg IM. The relative bioavailability of the capsule formulation compared to the solution is 100%. The mean elimination half-life of trimethobenzamide is 7 to 9 hours. Between 30 – 50% of a single dose in humans is excreted unchanged in the urine within 48 – 72 hours. The metabolic disposition of trimethobenzamide in humans is not known. Specifically, it is not known if active metabolites are generated in humans.

Special Populations

Age

The clearance of trimethobenzamide is not known in patients with renal impairment. However, it may be advisable to consider reduction in the dosing of trimethobenzamide in elderly patients with renal impairment considering that a substantial amount of excretion and elimination of trimethobenzamide occurs via the kidney and that elderly patients may have various degrees of renal impairment. (See PRECAUTIONS: General and DOSAGE AND ADMINISTRATION).

Gender

Systemic exposure to trimethobenzamide was similar between men (N=40) and women (N=28).

Race

Pharmacokinetics appeared to be similar for Caucasians (N=53) and African Americans (N=12).

Renal Impairment

The clearance of trimethobenzamide is not known in patients with renal impairment. However, it may be advisable to consider reduction in the dosing of trimethobenzamide in patients with renal impairment considering that a substantial amount of excretion and elimination of trimethobenzamide occurs via the kidney. (See PRECAUTIONS: General and DOSAGE AND ADMINISTRATION).

INDICATIONS

Tigan® is indicated for the treatment of postoperative nausea and vomiting and for nausea associated with gastroenteritis.

CONTRAINDICATIONS

The injectable form of Tigan® is contraindicated in pediatric patients and in patients with known hypersensitivity to trimethobenzamide.

WARNINGS

Tigan® may produce drowsiness. Patients should not operate motor vehicles or other dangerous machinery until their individual responses have been determined.

Usage in Pregnancy:

Trimethobenzamide hydrochloride was studied in reproduction experiments in rats and rabbits and no teratogenicity was suggested. The only effects observed were an increased percentage of embryonic resorptions or stillborn pups in rats administered 20 mg and 100 mg/kg and increased resorptions in rabbits receiving 100 mg/kg. In each study these adverse effects were attributed to one or two dams. The relevance to humans is not known. Since there is no adequate experience in pregnant or lactating women who have received this drug, safety in pregnancy or in nursing mothers has not been established.

Usage with Alcohol:

Concomitant use of alcohol with Tigan® may result in an adverse drug interaction.

PRECAUTIONS

During the course of acute febrile illness, encephalitides, gastroenteritis, dehydration and electrolyte imbalance, especially in children and the elderly or debilitated, CNS reactions such as opisthotonos, convulsions, coma and extrapyramidal symptoms have been reported with and without use of Tigan® (trimethobenzamide hydrochloride) or other antiemetic agents. In such disorders caution should be exercised in administering Tigan®, particularly to patients who have recently received other CNS-acting agents (phenothiazines, barbiturates, belladonna derivatives). Primary emphasis should be directed toward the restoration of body fluids and electrolyte balance, the relief of fever and relief of the causative disease process. Overhydration should be avoided since it may result in cerebral edema.

The antiemetic effects of Tigan® may render diagnosis more difficult in such conditions as appendicitis and obscure signs of toxicity due to overdosage of other drugs.

General

Adjustment of Dose in Renal Failure

A substantial route of elimination of unchanged trimethobenzamide is via the kidney. Dosage adjustment should be considered in patients with reduced renal function including some elderly patients. (See CLINICAL PHARMACOLOGY and DOSAGE AND ADMINISTRATION).

Geriatric Use

Clinical studies of trimethobenzamide hydrochloride did not include sufficient numbers of patients aged 65 and over to determine whether they respond differently from younger patients. Although there are studies reported in the literature that include elderly patients > 65 years old with younger patients, it is not known if there are differences in efficacy or safety parameters for elderly and non-elderly patients treated with trimethobenzamide. In general, dose selection for an elderly patient should be cautious, usually starting at the low end of the dosing range, reflecting the greater frequency of decreased hepatic, renal, or cardiac function, and of concomitant disease or other drug therapy.

This drug is known to be substantially excreted by the kidney, and the risk of toxic reactions to this drug may be greater in patients with impaired renal function. Because elderly patients are more likely to have decreased renal function, care should be taken in dose selection, and it may be useful to monitor renal function. (See CLINICAL PHARMACOLOGY and DOSAGE AND ADMINISTRATION).

ADVERSE REACTIONS

There have been reports of hypersensitivity reactions and Parkinson-like symptoms. There have been instances of hypotension reported following parenteral administration to surgical patients. There have been reports of blood dyscrasias, blurring of vision, coma, convulsions, depression of mood, diarrhea, disorientation, dizziness, drowsiness, headache, jaundice, muscle cramps and opisthotonos. If these occur, the administration of the drug should be discontinued. Allergic-type skin reactions have been observed; therefore, the drug should be discontinued at the first sign of sensitization. While these symptoms will usually disappear spontaneously, symptomatic treatment may be indicated in some cases.

For medical advice about adverse reactions contact your medical professional. To report SUSPECTED ADVERSE REACTIONS, contact Endo at 1-800-828-9393 or FDA at 1-800-FDA-1088 (1-800-332-1088) or www.fda.gov/medwatch.

DOSAGE AND ADMINISTRATION

(See WARNINGS and PRECAUTIONS.)

Dosage should be adjusted according to the indication for therapy, severity of symptoms and the response of the patient.

Geriatric Patients

Dose adjustment such as reducing the total dose administered at each dosing or increasing the dosing interval should be considered in elderly patients with renal impairment (creatinine clearance ≤ 70 mL/min/1.73m^2). Final dose adjustment should be based upon integration of clinical efficacy and safety considerations. (See CLINICAL PHARMACOLOGY and PRECAUTIONS).

Patients with Renal Impairment

In subjects with renal impairment (creatinine clearance ≤ 70 mL/min/1.73m^2), dose adjustment such as reducing the total dose administered at each dosing or increasing the dosing interval should be considered. (See CLINICAL PHARMACOLOGY and DOSAGE AND ADMINISTRATION).

INJECTABLE, 100 mg/mL (Not for use in pediatric patients)
Usual Adult Dosage
2 mL (200 mg) t.i.d. or q.i.d. intramuscularly.

NOTE: The injectable form is intended for intramuscular administration only; it is not recommended for intravenous use.

Intramuscular administration may cause pain, stinging, burning, redness and swelling at the site of injection. Such effects may be minimized by deep injection into the upper outer quadrant of the gluteal region, and by avoiding the escape of solution along the route.

STORAGE

Store between 20°C to 25°C (68°F to 77°F).

(See USP Controlled Room Temperature.)

HOW SUPPLIED

Tigan® (trimethobenzamide hydrochloride) is available as follows:

NDC 42023-119-25 200 mg/2mL (100 mg/mL) in 2 mL Single-Dose Vials. Discard Unused Portion. Pack of 25

Rx Only

Manufactured for:
Endo USA
Malvern, PA 19355

© 2025 Endo, Inc. or one of its affiliates.

Revised: 11/2025

PRINCIPAL DISPLAY PANEL - 200 mg/2 mL Carton

NDC 42023-119-25

Tigan®
(trimethobenzamide hydrochloride) Injection

200 mg/2 mL

(100 mg/mL)

For Intramuscular Use Only

2 mL Single Dose Vial